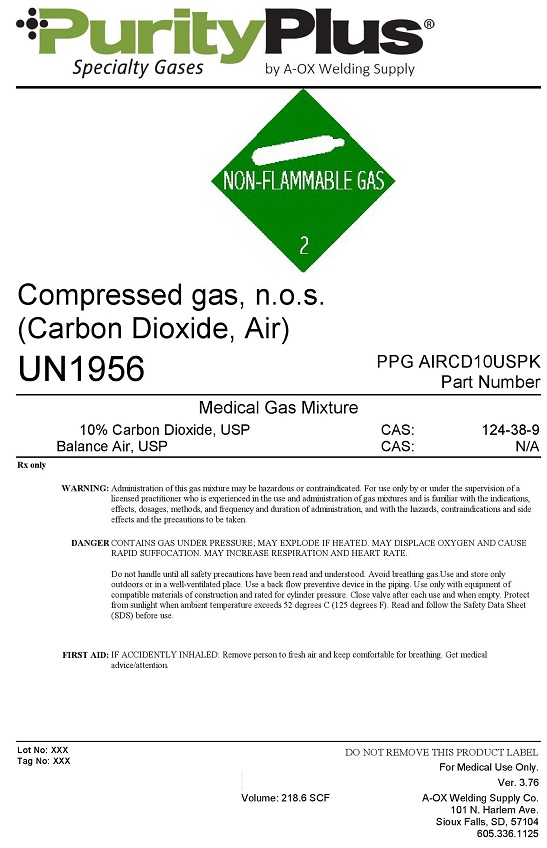 DRUG LABEL: Air 90% Carbon Dioxide 10%
NDC: 10297-400 | Form: GAS
Manufacturer: A-OX Welding Supply, LLC
Category: prescription | Type: HUMAN PRESCRIPTION DRUG LABEL
Date: 20251023

ACTIVE INGREDIENTS: CARBON DIOXIDE 100 mL/1 L
INACTIVE INGREDIENTS: OXYGEN 189 mL/1 L; NITROGEN 711 mL/1 L

Air 90% Carbon Dioxide 10% -400

PACKAGE LABEL

Purity Plus Specialty Gases by A-OX Welding Supply NON-FLAMMABLE GAS 2 Compressed gas, n.o.s. (Carbon Dioxide, Air) UN1956 PPG AIRCD10USPK
Medical Gas Mixture 10% Carbon Dioxide, USP CAS: 124-38-9 Balance Air, USP CAS: N/A
Rx only WARNING: Administration of this gas mixture may be hazardous or contraindicated. For use only by or under the supervision of a licensed practitioner who is experienced in the use and administration of gas mixtures and is familiar with the indications, effects, dosages, methods, and frequency and duration of administration, and with the hazards, contraindications, and side effects and the precautions to be taken.
DANGER: CONTAINS GAS UNDER PRESSURE; MAY EXPLODE IF HEATED. MAY DISPLACE OXYGEN AND CAUSE RAPID SUFFOCATION. MAY INCREASE RESPIRATION AND HEART RATE.
Do not handle until all safety precautions have been read and understood. Avoid breathing gas. Use and store only outdoors or in a well-ventilated place. Use a back flow preventive device in the piping. Use only with equipment of compatible materials of construction and rated for cylinder pressure. Close valve after each use and when empty. Protect from sunlight when Protect from sunlight when ambient temperature exceeds 52 degrees C (125 degrees F). Read and follow the Safety Data Sheet (SDS) before use. FIRST AID: IF ACCIDENTLY INHALED: Remove person to fresh air and keep comfortable for breathing. Get medical advice/attention.
Lot No: XXX Tag No: XXX DO NOT REMOVE THIS PRODUCT LABEL For Medical Use Only. Ver. 3.76 Volume: 218.6 SCF A-OX Welding Co. 101 N Harlem Ave. Sioux Falls, SD 57104 605.336.1125